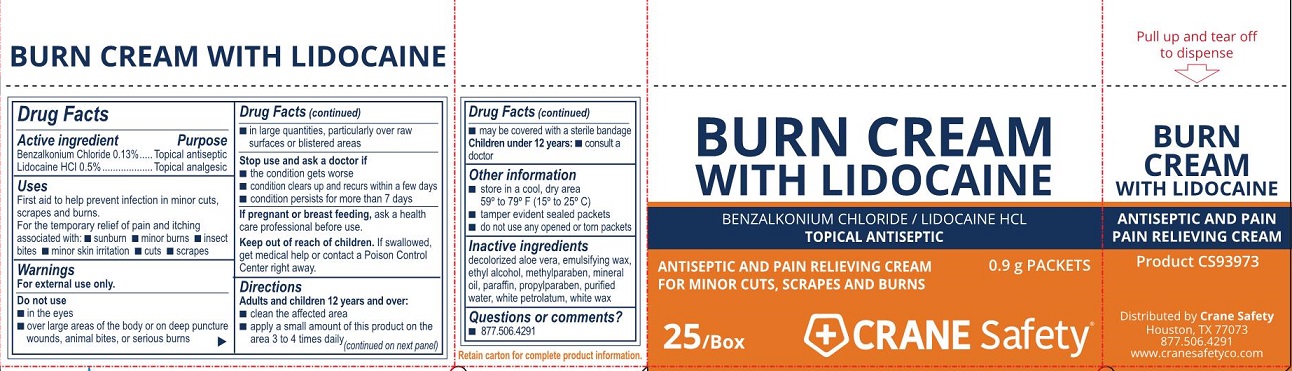 DRUG LABEL: Crane Safety Burn
NDC: 73408-260 | Form: CREAM
Manufacturer: Crane Safety LLC
Category: otc | Type: HUMAN OTC DRUG LABEL
Date: 20240116

ACTIVE INGREDIENTS: LIDOCAINE HYDROCHLORIDE 5 mg/1 g; BENZALKONIUM CHLORIDE 1.3 mg/1 g
INACTIVE INGREDIENTS: METHYLPARABEN; PROPYLPARABEN; WATER; WHITE WAX; MINERAL OIL; ALOE VERA LEAF; ALCOHOL; PARAFFIN; PETROLATUM

Crane Safety Burn Cream

Active ingredients

Benzalkonium chloride 0.13%

Lidocaine HCl 0.5%

Purpose

Topical antiseptic

Topical analgesic

Uses

First aid to help prevent infection in minor cuts, scrapes and burns.

For temporary relief of pain and itching associated with:

- sunburn
- minor burns
- insect bites
- minor skin irritation
- cuts
- scrapes

Warnings

For external use only.

Do not use

- in the eyes
- over large areas of the body or on deep puncture wounds, animal bites or serious burns
- in large quantities, particularly over raw surfaces or blistered areas

Stop use and ask a doctor if

- condition gets worse
- condition clears up and recurs within a few days
- condition persists for more than 7 days

If pregnant or breast feeding,

ask a health professional before use.

Keep out of reach of children.

If swallowed, get medical help or contact a Poison Control Center right away.

Directions

Adults and children 12 years and over:

- clean the affected area
- apply a small amount of this product on the area 3 to 4 times daily
- may be covered with a sterile bandage

Children under 12 years:

consult a doctor

Other information

- store in a cool, dry area
- 59° to 79° F (15° to 25° C)
- tamper evident sealed packets
- do not use any open or torn packets

Inactive ingredients

decolorized aloe vera, emulsifying wax, ethyl alcohol, methylparaben, mineral oil, paraffin, propylparaben, purified water, white petrolatum, white wax

Questions or comments?

877.506.4291

Crane Safety Burn Cream Label

Burn Cream with Lidocaine

Benzalkonium Chloride / Lidocaine HCl

Topical Antiseptic

Antiseptic and Pain relieving Cream for Minor Cuts, Scrapes and Burns

0.9 g Packets

25/Box

CRANE Safety®